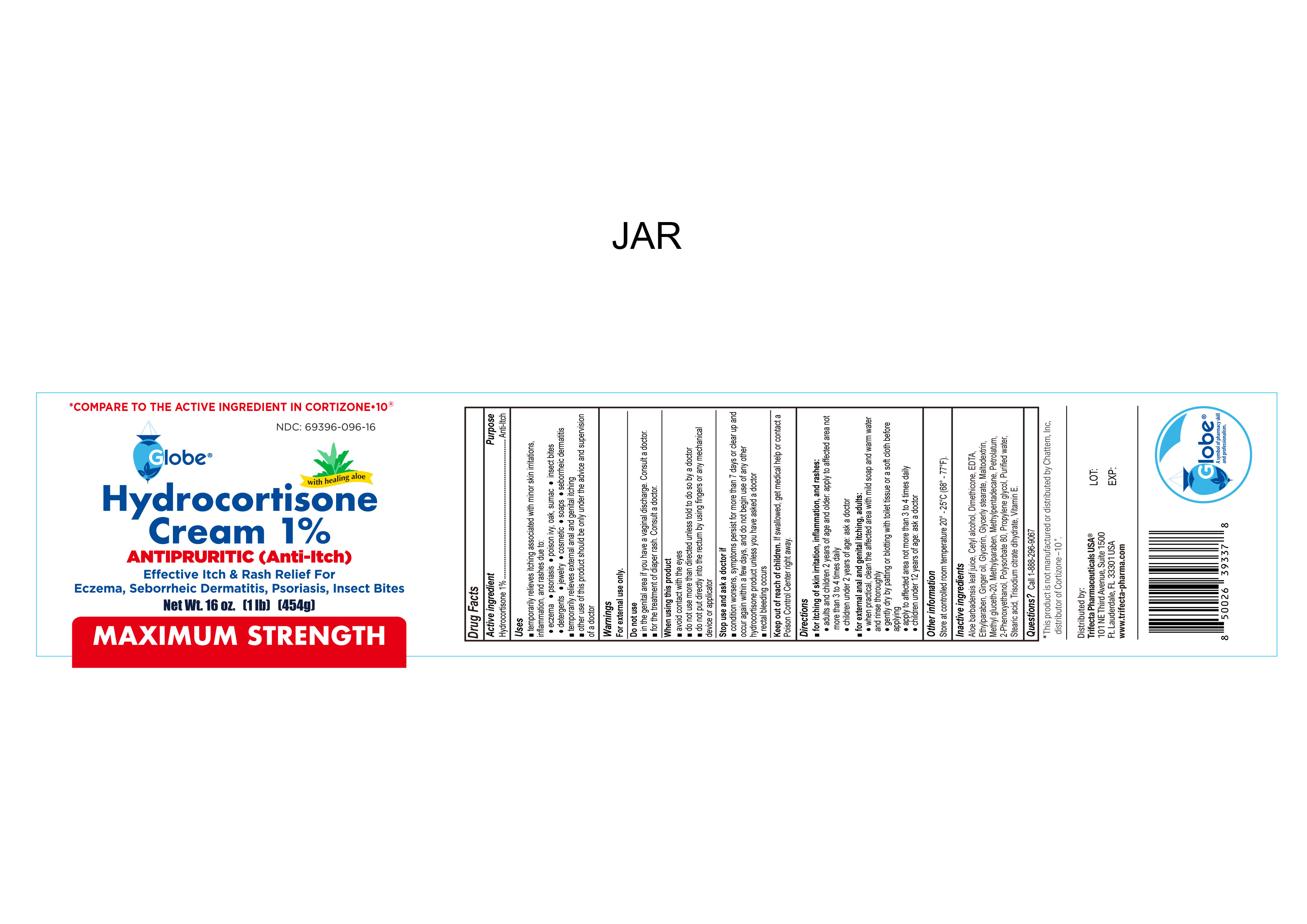 DRUG LABEL: Hydrocortisone Cream
NDC: 69396-096 | Form: CREAM
Manufacturer: Trifecta Pharmaceuticals USA
Category: otc | Type: HUMAN OTC DRUG LABEL
Date: 20250508

ACTIVE INGREDIENTS: HYDROCORTISONE 1 g/100 g
INACTIVE INGREDIENTS: EDETIC ACID; MALTODEXTRIN; GINGER OIL; POLYSORBATE 80; STEARIC ACID; METHYL GLUCETH-20; 3-METHYLPENTADECANE; PHENOXYETHANOL; ETHYLPARABEN; DIMETHICONE; GLYCERIN; GLYCERYL MONOSTEARATE; PETROLATUM; ALOE VERA LEAF; CETYL ALCOHOL; WATER; TRISODIUM CITRATE DIHYDRATE; METHYLPARABEN; PROPYLENE GLYCOL; .ALPHA.-TOCOPHEROL

Hydrocortisone Cream 1%

Active Ingredient

Hydrocortisone 1%

Purpose

Anti-Itch

Uses

For temporarily rellief of itching associated with minor skin irritations, inflammation and rashes due to:

- eczema
- seborrheic dermatitis
- psoriasis
- insect bites
- poison ivy
- poison oak
- poison sumac
- soaps
- detergents
- cosmetics
- jewelry
- temporarily relieves external anal and genital itching

Other use of this product should be only under the advice and supervision of a doctor

Keep out of reach of children

If swallowed, get medical help or contact a Poison Control Center immediately.

Warnings

- for external use only

Stop using this product and ask a doctor

- Conditions worsen, symptoms persist for more than 7 days or clear up and occur again within a few days. Do not begin use of any other hydrocortisone product unless you have asked a doctor.
- Rectal bleeding occurs

When using this product

- avoid contact with the eyes
- Do not use more than directed unless told to do so by a doctor
- Do not put directly into the rectum by using fingers or any mechanical device or applicator.

Do not use

- In the genital area if you have a vaginal discharge. Consult a doctor.
- For the treatment of diaper rash, Consult a doctor.

Directions

For itching of skin irritation, inflammation, and rashes:

Adults and Children 2 years and older

- Apply to affected area not more than 3 to 4 times daily.

Children under 2 years of age: ask a doctor

For external anal and genital itching, adults:

- When practical, clean the affected area with mild soap and warm water and rinse thoroughly.
- gently dry by patting or blotting with toilet tissue or a soft cloth before applying.
- Apply to affected area not more than 3 to 4 times daily

- Children under 12 years of age; ask a doctor.

Inactive Ingredients

Aloe barbadensis leaf juice, Cetyl alcohol, Dimethicone, EDTA, Ethylparaben, Ginger Oil, glycerin, Glycerol Stearate, Maltodextrin, Methyl gluceth-20, Methylparaben, Methylpentadecane, petrolatum, 2-Phenoxyethanol, Polysorbate 80, Propylene Glycol, purified water, Stearic Acid, Trisodium citrate dihydrate, Vitamin E.

Other Information

- store at controlled room temperature 20°- 25°C (68°-77°F)

Questions

Call 1-888-296-9067

Other Information

Distributed By:

Trifecta Pharmaceuticals USA®

101 NE Third Avenue, Suite 1500

Ft. Lauderdale, FL. 33301 USA

www.trifecta-pharma.com

This product is not manufactured or distributed by Chattem, Inc. distributor of Cortizone-10.